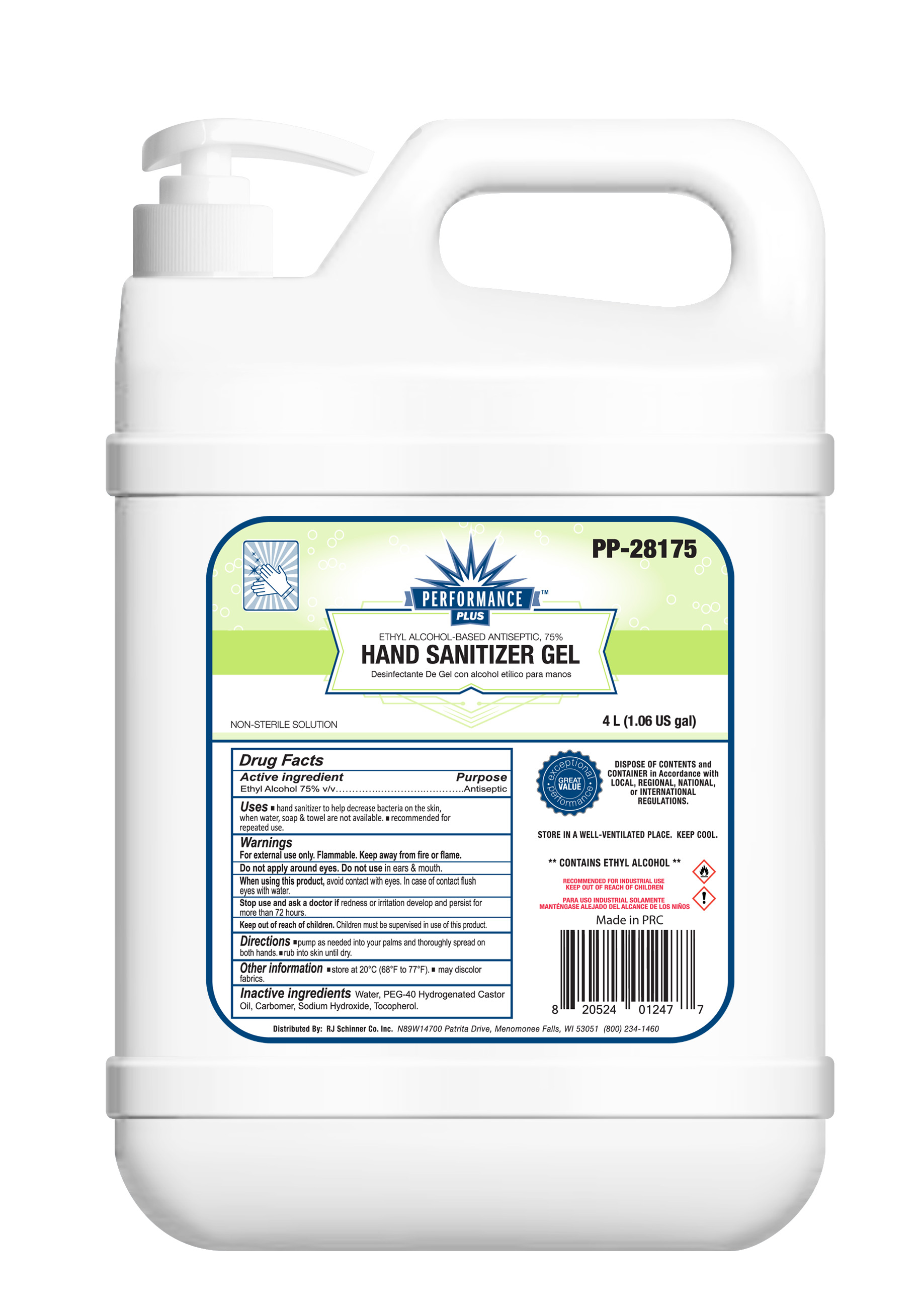 DRUG LABEL: FOCAN LLC PERFORMANCE PLUS Hand Sanitizer Gel
NDC: 74913-444 | Form: GEL
Manufacturer: SHANTOU S.E.Z BAOJIE INDUSTRY CO., LTD
Category: otc | Type: HUMAN OTC DRUG LABEL
Date: 20200613

ACTIVE INGREDIENTS: ALCOHOL 75 mL/100 mL
INACTIVE INGREDIENTS: SODIUM HYDROXIDE 0.3 mL/100 mL; PEG-40 CASTOR OIL 0.5 mL/100 mL; TOCOPHEROL 0.5 mL/100 mL; WATER 23.2 mL/100 mL; CARBOMER 940 0.5 mL/100 mL

FOCAN LLC PERFORMANCE PLUS HAND SANITIZER GEL

Active Ingredient(s)

Alcohol :62% v/v. Purpose: Antiseptic

Purpose

Antiseptic, Hand Sanitizer

Use

Hand Sanitizer to help reduce bacteria that potentially can cause disease. For use when soap and water are not available.

Warnings

For external use only. Flammable. Keep away from heat or flame

Do not use

- in children less than 2 months of age
- on open skin wounds

When using this product keep out of eyes, ears, and mouth. In case of contact with eyes, rinse eyes thoroughly with water.

Stop use and ask a doctor if irritation or rash occurs. These may be signs of a serious condition.

Keep out of reach of children. If swallowed, get medical help or contact a Poison Control Center right away.

Directions

- Place enough product on hands to cover all surfaces. Rub hands together until dry.
- Supervise children under 6 years of age when using this product to avoid swallowing.

Other information

- Store between 15-30C (59-86F)
- Avoid freezing and excessive heat above 40C (104F)

Inactive ingredients

WATER, PEG-40 CASTOR OIL, CARBOMER 940, SODIUM HYDROXIDE, TOCOPHEROL